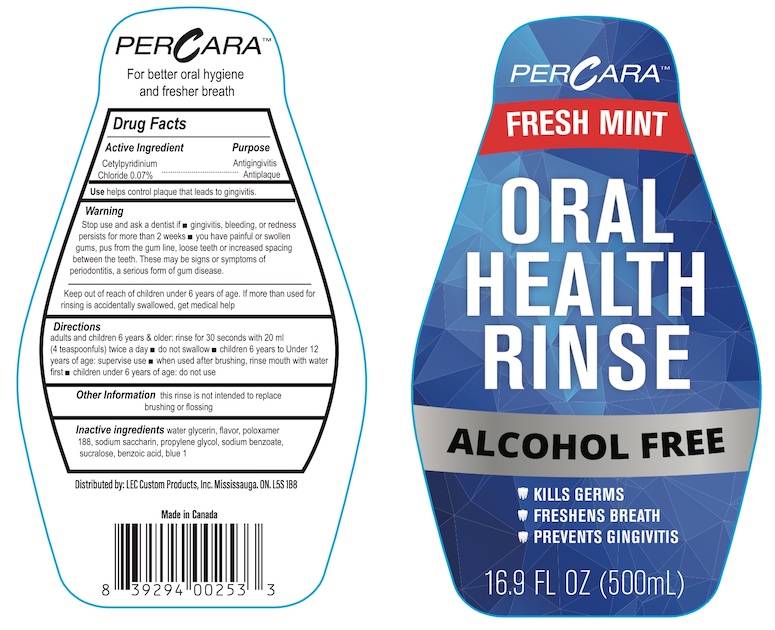 DRUG LABEL: PerCara Oral Health Rinse
NDC: 67933-0321 | Form: RINSE
Manufacturer: LEC Custom Products, Inc
Category: otc | Type: HUMAN OTC DRUG LABEL
Date: 20240101

ACTIVE INGREDIENTS: CETYLPYRIDINIUM CHLORIDE 0.07 g/100 mL
INACTIVE INGREDIENTS: SODIUM BENZOATE; SUCRALOSE; WATER; BENZOIC ACID; POLOXAMER 188; GLYCERIN; SACCHARIN SODIUM; FD&C BLUE NO. 1; PROPYLENE GLYCOL

PerCara Fresh Mint Oral Health Rinse

Drug Facts

Active Ingredient
Cetylpyridinium chloride 0.07%

Purpose

Antigingivitis

Antiplaque

INDICATIONS AND USAGE

Use helps control plaque that leads to gingivitis.

Warning

Stop use and ask a dentist if

- gingivitis, bleeding, or redness persists for more than 2 weeks
- you have painful or swollen gums, pus from the gum line, loose teeth or increased spacing between the teeth. These may be symptoms of periodontitis, a serious form of gum disease.

Keep out of reach of children under 6 years of age. If more than used for rinsing is accidentally swallowed, get medical help.

Directions

- adults and children 6 years & older: rinse for 30 seconds with 20 mL (4 teaspoonfuls) twice a day
- do not swallow
- children 6 to Under 12 years of age: supervise use
- when used after brushing. rinse mouth with water first
- children under 6 years of age: do not use

Other Information

this rinse is not intended to replace brushing or flossing

INACTIVE INGREDIENT

Inactive Ingredients water, glycerin, flavor, poloxamer 188, sodium saccharin, propylene glycol, sodium benzoate, sucralose, benzoic acid, blue 1

Distributed by: LEC Custom Products, Inc. Mississauga, ON. L5S 1B8

Made in Canada

PACKAGE LABEL

PERCARA™

FRESH MINT

ORAL HEALTH RINSE

ALCOHOL FREE

KILLS GERMS

FRESHENS BREATH

PREVENTS GINGIVITIS

16.9 FL OZ (500mL)